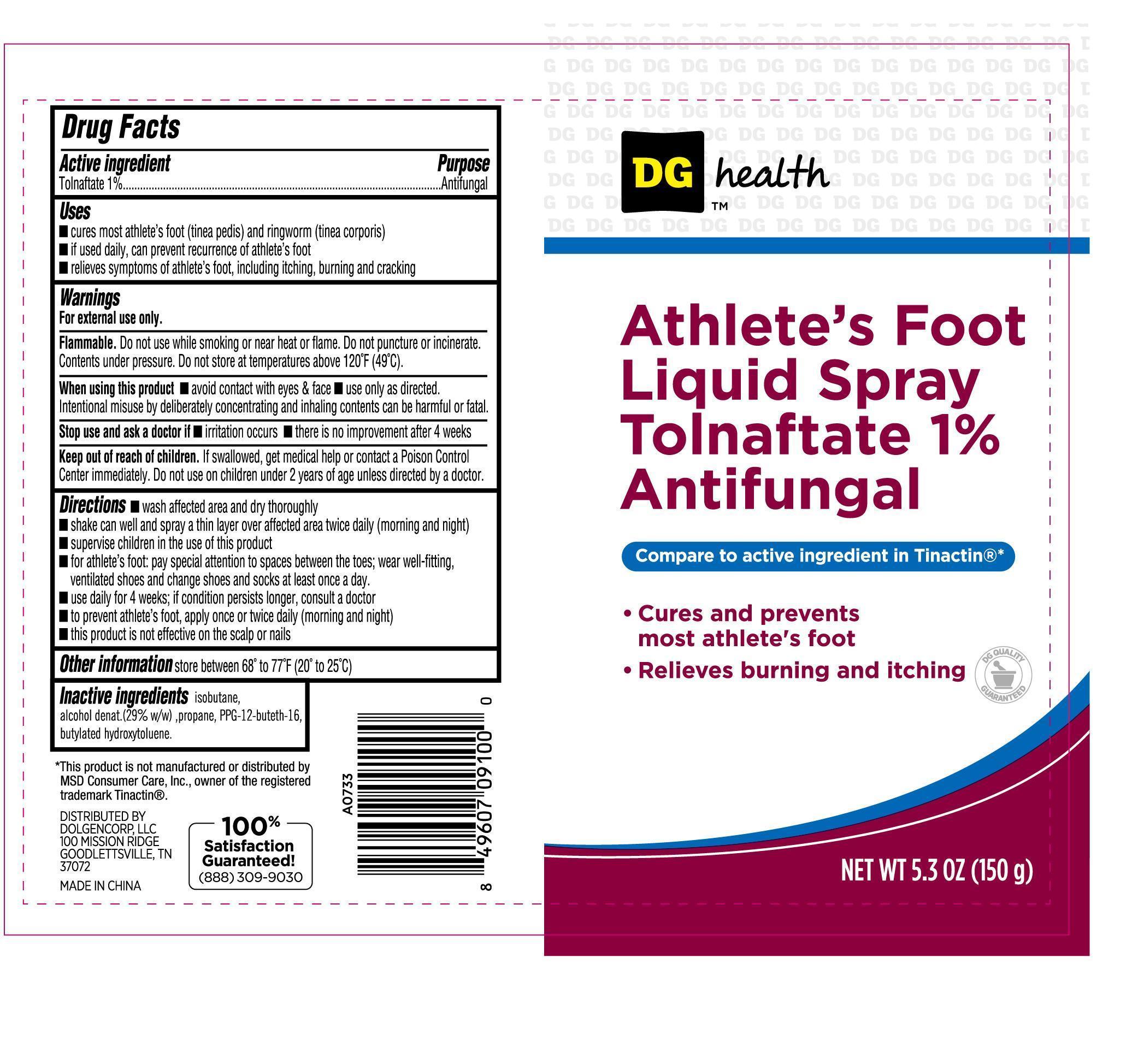 DRUG LABEL: Athletes Foot
NDC: 55910-007 | Form: SPRAY
Manufacturer: DOLGENCORP, LLC.
Category: otc | Type: HUMAN OTC DRUG LABEL
Date: 20181221

ACTIVE INGREDIENTS: TOLNAFTATE 1 g/100 g
INACTIVE INGREDIENTS: ISOBUTANE; ALCOHOL; PROPANE; PPG-12-BUTETH-16; BUTYLATED HYDROXYTOLUENE

Athletes Foot

Active IngredientPurpose

Tolnaftate 1% ................................................................ Antifungal

Uses

- cures most athlete's foot (tinea pedis) and ringworm (tinea corporis)
- if used daily, can prevent recurrence of athlete's foot
- relieves symptoms of athlete's foot, including itching, burning and cracking

Keep out of reach of children. If swallowed, get medical help or contact a Poison Control Center immediately. Do not use on children under 2 years of age unless directed by a doctor.

INDICATIONS AND USAGE

DG Health

Athlete's Foot Liquid Spray Tolnaftate 1% Antifungal

Compare to active ingredeint in Tinactin®*

Cures and prevents most athlete's foot

Relieves burning and itching

Net Wt 5.3oz (150g)

Warnings

For external use only.

Flammable. Do not use while smoking or near heat or flame. Do not puncture or incinerate. Contents under pressure. Do not store at temperatures above 120oF (49oC).

When using this product

- avoid contact with eyes and face
- use only as directed. Intentional misuse by deliberately concentrating and inhaling contents can be harmful or fatal

Stop use and ask a doctor if

- irritation occurs
- there is no improvement after 4 weeks

Directions

- wash affected area and dry thoroughly
- shake can well and spray a thin layer over affected area twice daily (morning and night)
- supervise children in the use of this product
- for athlete's foot: pay special attention to spaces between the toes; wear well-fitting, ventilated shoes and change shoes and socks at least once a day
- use daily for 4 weeks; if condition persists longer, consult a doctor
- to prevent athlete's foot, apply once or twice daily (morning and night)
- this product is not effective on the scalp or nails

Inactive Ingredients

isobutane, alcohol denat. (29% w/w), propane, PPG-12-buteth-16, butylated hydroxytoluene